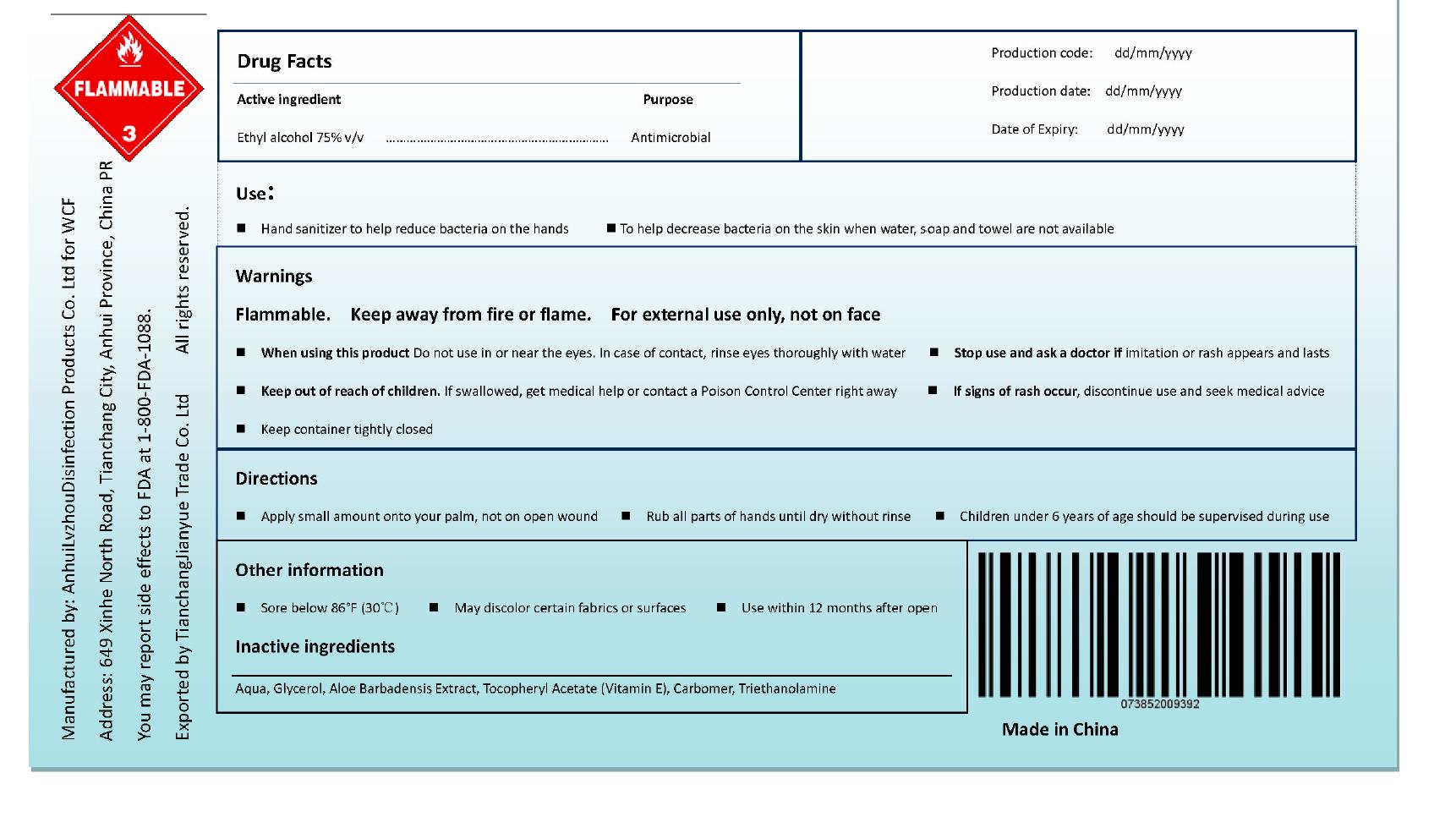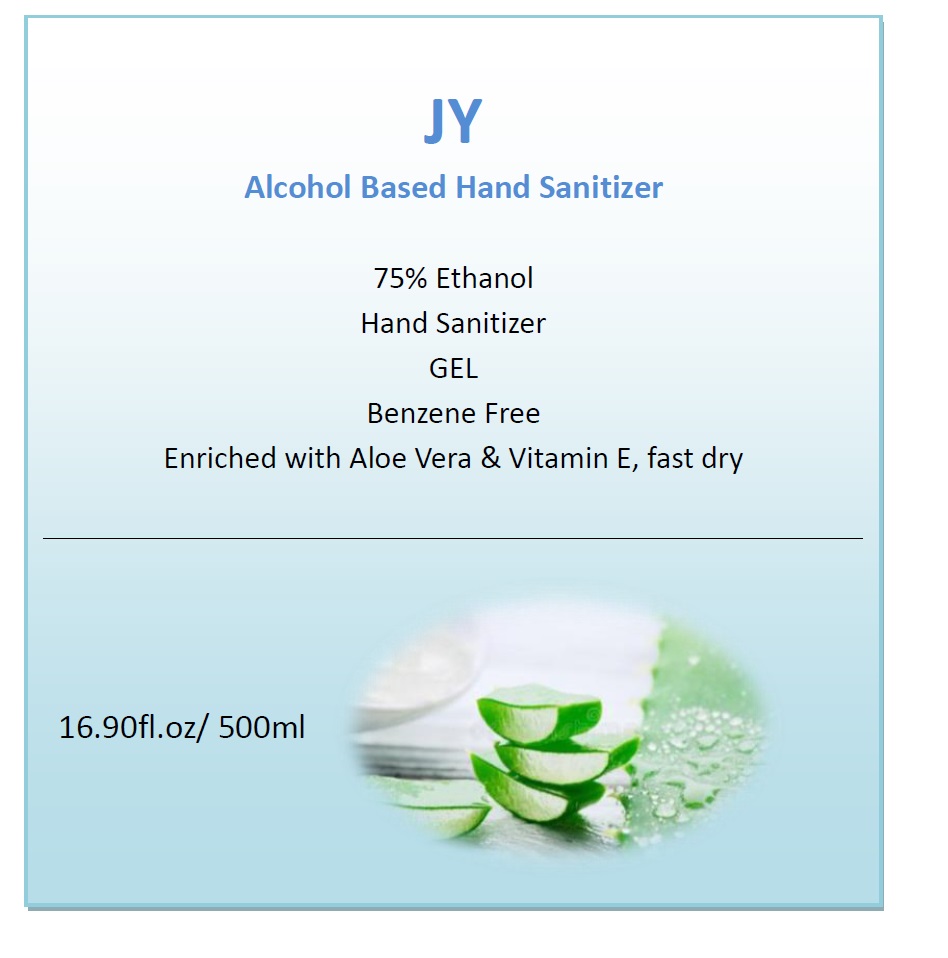 DRUG LABEL: Hand Sanitizer
NDC: 52985-901 | Form: GEL
Manufacturer: Anhui Oasis Disinfection Products Co., Ltd
Category: otc | Type: HUMAN OTC DRUG LABEL
Date: 20220114

ACTIVE INGREDIENTS: ALCOHOL 75 mL/100 mL
INACTIVE INGREDIENTS: CARBOMER HOMOPOLYMER, UNSPECIFIED TYPE; ALOE VERA LEAF; WATER; TROLAMINE; GLYCERIN; ALPHA-TOCOPHEROL ACETATE

52985-901 Hand Sanitizer Gel 75% Alcohol

Active Ingredient

Ethyl Alcohol 75%

Purpose

Antimicrobial

Use

Hand sanitizer to help reduce bacteria on the hands
To help decrease bacteria on the skin when water, soap and towel are not available

WARNINGS

Flammable. Keep away from fire or flame. For external use only, not on face
■When using this product Do not use in or near the eyes. In case of contact, rinse eyes thoroughly with water ■ Stop use and ask a doctor if imitation or rash appears and lasts

■Keep out of reach of children. If swallowed, get medical help or contact a Poison Control Center right away
1 If signs of rash occur, discontinue use and seek medical advice
■Keep container tightly closed

Directions

■Apply small amount onto your palm, not on open wound

■Rub all parts of hands until dry without rinse
Children under 6 years of age should be supervised during use
Other information
Sore below 86°F (30°C)
1 May discolor certain fabrics or surfaces
■Use within 12 months after open

Inactive ingredients

Aqua, Glycerol, Aloe Barbadensis Extract, Tocopheryl Acetate (Vitamin E), Carbomer, Triethanolamine